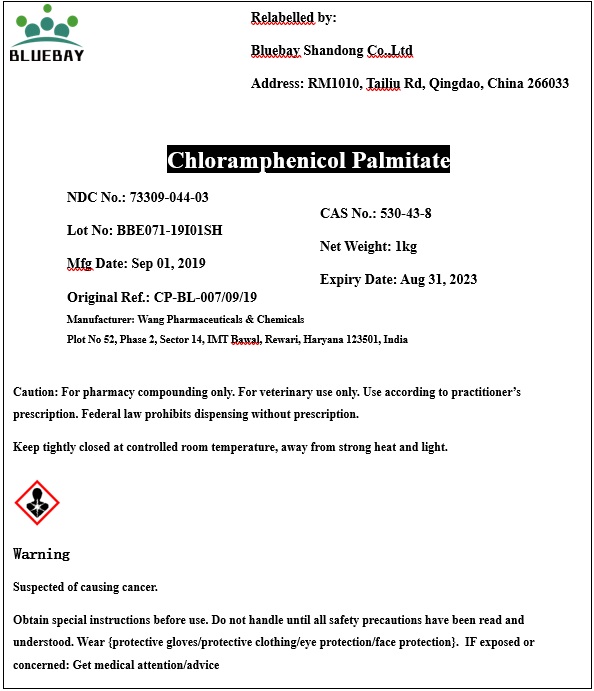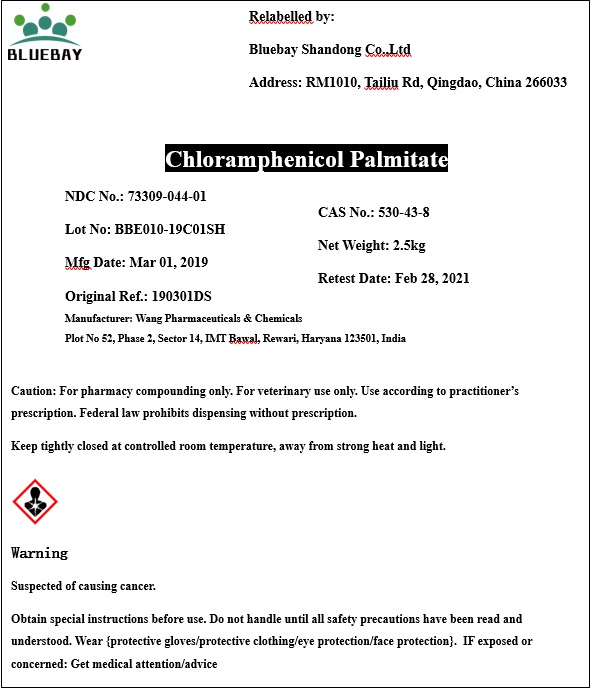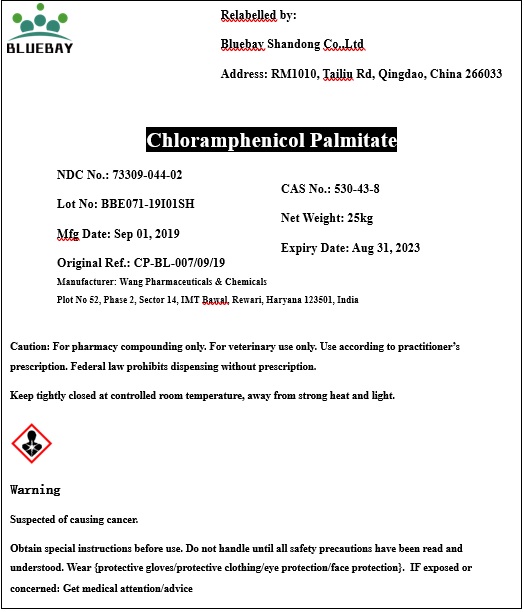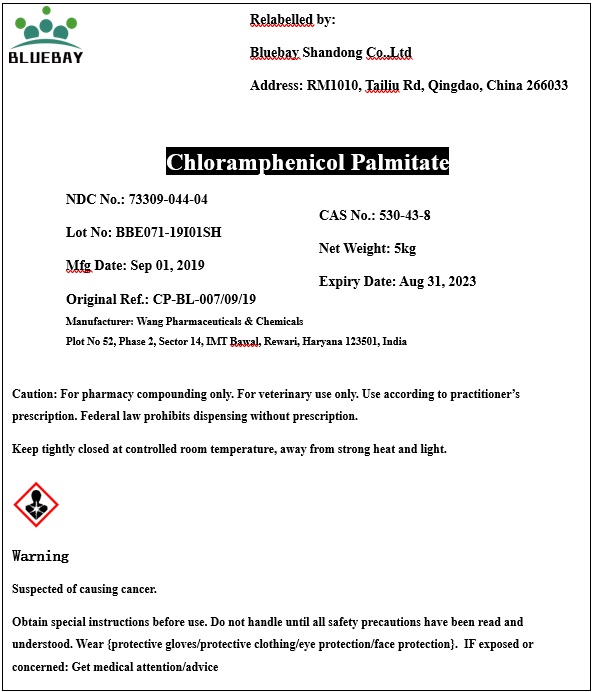 DRUG LABEL: Chloramphenicol Palmitate
NDC: 73309-044 | Form: POWDER
Manufacturer: BLUEBAY SHANDONG CO.,LTD
Category: other | Type: BULK INGREDIENT
Date: 20191022

ACTIVE INGREDIENTS: CHLORAMPHENICOL PALMITATE 1 kg/1 kg

Chloramphenicol Palmitate